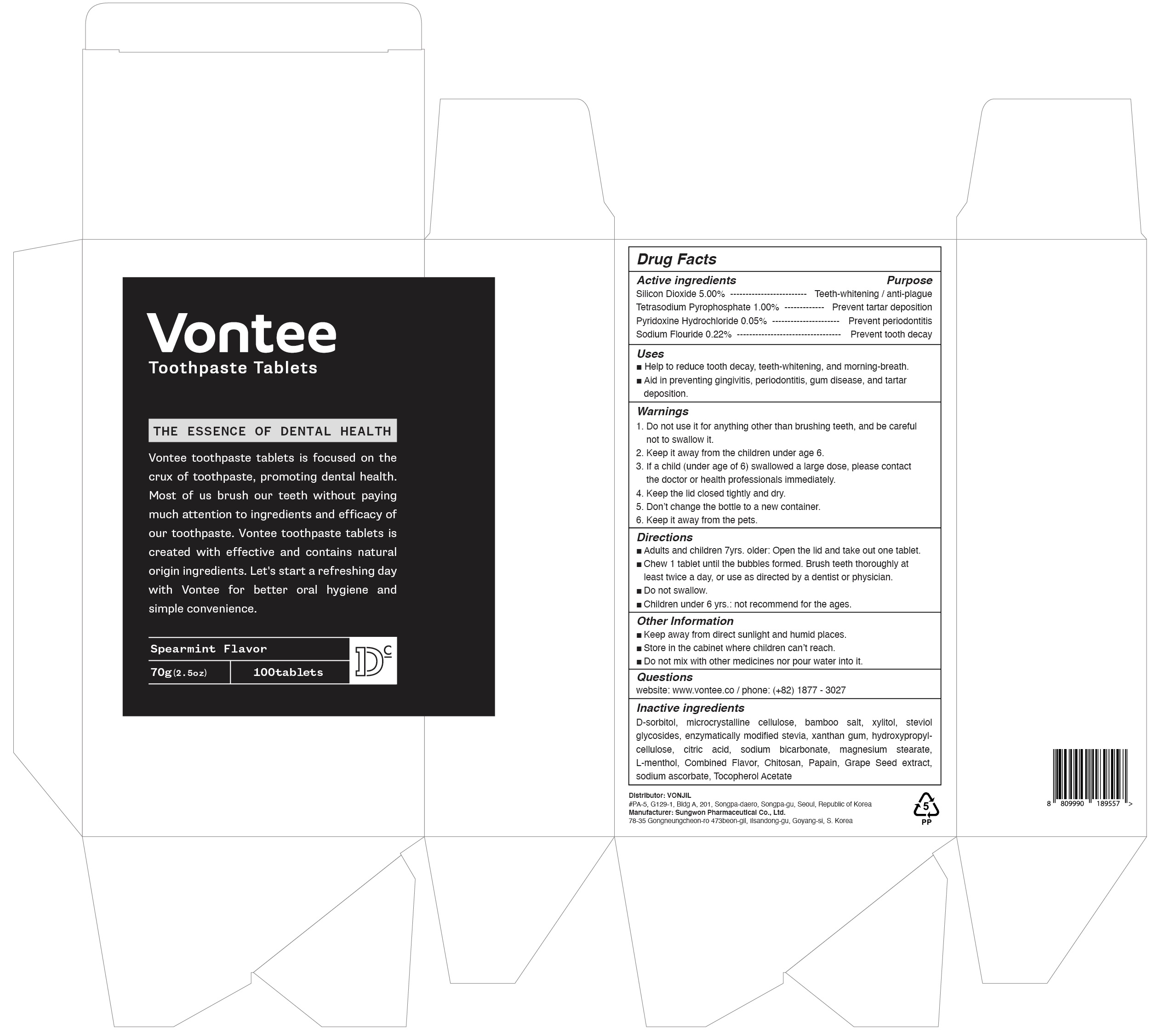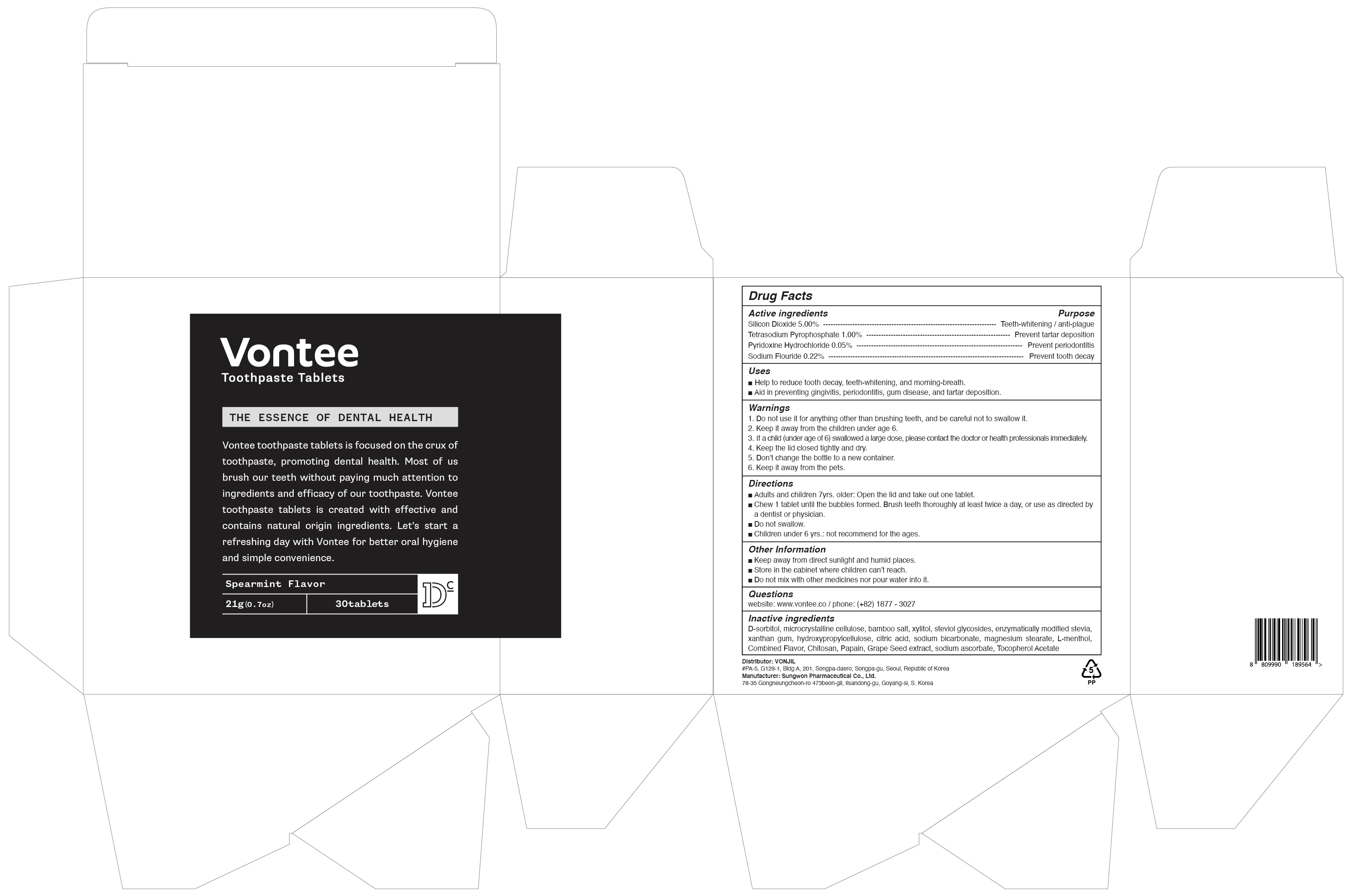 DRUG LABEL: Vontee
NDC: 80687-010 | Form: TABLET
Manufacturer: VONJIL
Category: otc | Type: HUMAN OTC DRUG LABEL
Date: 20201021

ACTIVE INGREDIENTS: SILICON DIOXIDE 5.0 g/100 g; SODIUM PYROPHOSPHATE 1.0 g/100 g; PYRIDOXINE HYDROCHLORIDE 0.05 g/100 g; SODIUM FLUORIDE 0.22 g/100 g
INACTIVE INGREDIENTS: SORBITOL; Xylitol

ACTIVE INGREDIENTS

Silicon Dioxide 5.00%
Tetrasodium Pyrophosphate 1.00%
Pyridoxine Hydrochloride 0.05%
Sodium Fluoride 0.22%

INACTIVE INGREDIENTS

D-sorbitol, microcrystalline cellulose, bamboo salt, xylitol, steviol glycosides, enzymatically modified stevia, xanthan gum, hydroxypropylcellulose, citric acid, sodium bicarbonate, magnesium stearate, L-menthol, Combined Flavor, Chitosan, Papain, Grape Seed extract, sodium ascorbate, Tocopherol Acetate

PURPOSE

Teeth-whitening / anti-plague
Prevent tartar deposition
Prevent periodontitis
Prevent tooth decay

WARNINGS

1. Do not use it for anything other than brushing teeth, and be careful not to swallow it.
2. Keep it away from the children under age 6.
3. If a child (under age of 6) swallowed a large dose, please contact the doctor or health professionals immediately.
4. Keep the lid closed tightly and dry.
5. Don’t change the bottle to a new container.
6. Keep it away from the pets.

KEEP OUT OF REACH OF CHILDREN

Keep it away from the children under age 6.

If a child (under age of 6) swallowed a large dose, please contact the doctor or health professionals immediately.

Uses

■ Help to reduce tooth decay, teeth-whitening, and morning-breath.
■ Aid in preventing gingivitis, periodontitis, gum disease, and tartar deposition.

Directions

■ Adults and children 7yrs. older: Open the lid and take out one tablet.
■ Chew 1 tablet until the bubbles formed. Brush teeth thoroughly at least twice a day, or use as directed by a dentist or physician.
■ Do not swallow.
■ Children under 6 yrs.: not recommend for the ages.

Other Information

■ Keep away from direct sunlight and humid places.
■ Store in the cabinet where children can’t reach.
■ Do not mix with other medicines nor pour water into it.

QUESTIONS

website: www.vontee.co
phone: (+82) 1877 - 3027